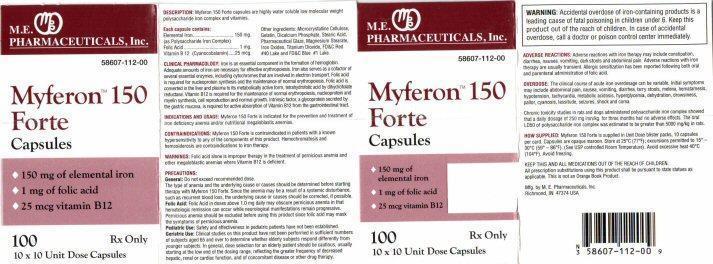 DRUG LABEL: Myferon 150 Forte
NDC: 58607-112 | Form: CAPSULE
Manufacturer: MARTIN EKWEALOR PHARMACEUTICALS, INC.
Category: prescription | Type: HUMAN PRESCRIPTION DRUG LABEL
Date: 20140220

ACTIVE INGREDIENTS: IRON SUCROSE 150 mg/1 1; FOLIC ACID 1 mg/1 1; CYANOCOBALAMIN 25 ug/1 1
INACTIVE INGREDIENTS: CELLULOSE, MICROCRYSTALLINE; GELATIN; CALCIUM PHOSPHATE, DIBASIC, ANHYDROUS; STEARIC ACID; SHELLAC; MAGNESIUM STEARATE; FERRIC OXIDE RED; TITANIUM DIOXIDE; FD&C RED NO. 40; FD&C BLUE NO. 1

DESCRIPTION:

Myferon 150 Forte capsules are highly water soluble low molecular weight polysaccharide iron complex and vitaminns.

Each capsule contains:

Elemental Iron .......... 150 mg
(as Polysaccharide Iron Complex)

Folic Acid .................. 1 mg

Vitamin B 12 ............... 25 mcg.
(Cyanocobalamin)

Other ingredients: Microcrystalline Cellulose, Gelatin, Dicalcium, Phosphate, Stearic Acid, Pharmaceutical Glaze, Magnesium Stearate, Iron Oxides, Titanium Dioxide, FD and C Red #40 Lake and FD and C Blue #1 Lake.

CLINICAL PHARMACOLOGY:

Iron is an essential component in the formation of hemoglobin. Adequate amounts of iron are necessary for effective erythropoiesis. Iron also serves as a cofactor of several enzymes, including cytochromes that are involved in electron transport. Folic acid is required for nucleoprotein synthesis and the maintenance of normal erythropoiesis. Folic acid is converted in the liver and plasma to its metabolically active form, tetrahydrofolic acid by dihydrofolate reductase. Vitamin B 12 is required for the maintenance of normal erythhropoiesis, nucleoprotein and myelin synthesis, cell reproduction and normal growth. Intrinsic factor, a glycoprotein secreted by the gastric mucosa, is required for active absorption of Vitamin B 12 from the gastric tract.

INDICATIONS AND USAGE:

Myferon 150 Forte is indicated for the prevention and treatment of iron deficiency anemia and/or nutritional megaloblastic anemias.

CONTRAINDICATIONS:

Myferon 150 Forte is contraindicated in patients with a known hypersensitivity to any of the components of this product. Hemochromatosis and hemosiderosis are contraindications to iron therapy.

WARNINGS:

Folic acid alone is improper therapy in the treatment of pernicious anemia and other megaloblastic anemias where Vitamin B 12 is deficient.

PRECAUTIONS:

General: Do not exceed recommended dose.

The type of anemia and the underlying cause or causes should be determined before starting therapy with Myferon 150 Forte. Since the anemia may be a result of a systemic disturbance, such as recurrent blood loss, the underlying cause or causes should be corrected. If possible.

Folic Acid: Folic Acid in doses above 1.0 mg daily may obscure pernicious anemia in that hematologic remission can occur while neurological manifestations remain progressive. Pernicious anemia should be excluded before using this product since folic acid may mask the symptoms of pernicious anemia.

Pediatric Use: Safety and effectiveness in pediatric patients have not been established.

Geriatric Use: Clinical studies on this product have not been performed in sufficient numbers of subjects aged 65 and over to determine whether elderly subjects respond differently from younger subjects. In general, dose selection for an elderly patient should be cautious, usually starting at the low end of the dosing range, reflecting the greater frequency of decreased hepatic, renal or cardiac function, and of concomitant disease or other drug therapy.

WARNING:

Accidental overdose of iron-containing products is a leading cause of fatal poisoning in children under 6. Keep this product out of the reach of children. In case of accidental overdose, call a doctor or poison control center immediately.

ADVERSE REACTIONS:

Adverse reactions with iron therapy may include constipation, diarrhea, nausea, vomiting, dark stools, and abdominal pain. Adverse reactions with iron therapy are usually transient. Allergic sensitization has been reported following both oral and parenteral administration of folic acid.

OVERDOSE:

The clinical course of acute iron overdosage can be variable. Initial symptoms may include abdominal pain, nausea, vomiting, diarrhea, tarry stools, melena, hematamesis, hypotension, tachycardia, metabolic acidosis, hyperglycemia, dehydration, drowsiness, pallor, cyanosis, lassitude, seizures, shock and coma.

Chronic toxicity studies in rats and dogs administered polysaccharide iron complex showed that a daily dosage of 250 mg iron/kg. for three months had no adverse effects. The oral LD50 of polysaccharide iron complex was estimated to be greater than 5000 mg/kg in rats.

HOW SUPPLIED:

Myferon 150 Forte is supplied in Unit Dose blister packs, 10 capsules per card. Capsules are opaque maroon. Store at 25° C (77° F); excursions permitted to 15° -30° C (59° -86° F). (See USP controlled Room Temperature). Avoid excessive heat 40° C (104° F). Avoid freezing.

KEEP THIS AND ALL MEDICATION OUT OF THE REACH OF CHILDREN.

All prescription substitutions using this product shall be pursuant to state statues as applicable. This is not an Orange Book Product.

Myferon 150 Forte Product Label

M.E. PHARMACEUTICALS, Inc.

58607-112-00

Myferon™ 150 Forte
Capsules

150 mg of elemental iron
1 mg of folic acid
25 mcg vitamin B12

100 Rx Only

10 x 10 Unit Dose Capsules

Mfg. by M.E. Pharmaceuticals, Inc.
Richmond, IN 47374 USA